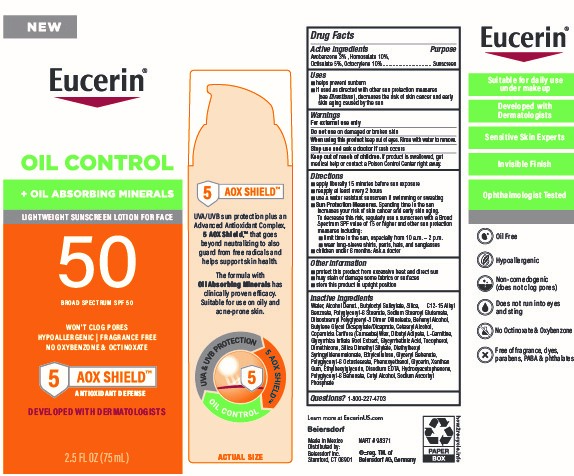 DRUG LABEL: Eucerin Oil-Control SPF 50 Sunscreen
NDC: 66800-6000 | Form: LOTION
Manufacturer: Beiersdorf Inc
Category: otc | Type: HUMAN OTC DRUG LABEL
Date: 20251231

ACTIVE INGREDIENTS: AVOBENZONE 3 g/100 g; HOMOSALATE 10 g/100 g; OCTISALATE 5 g/100 g; OCTOCRYLENE 10 g/100 g
INACTIVE INGREDIENTS: SODIUM ASCORBYL PHOSPHATE; LEVOCARNITINE; ENOXOLONE; GLYCYRRHIZA ECHINATA ROOT; SILICA DIMETHYL SILYLATE; DIETHYLHEXYL SYRINGYLIDENEMALONATE; POLYGLYCERYL-6 BEHENATE; BUTYLENE GLYCOL DICAPRYLATE/DICAPRATE; COPERNICIA PRUNIFERA WHOLE; ETHYLCELLULOSES; PHENOXYETHANOL; GLYCERIN; WATER; DIBUTYL ADIPATE; TOCOPHEROL; DIMETHICONE; EDETATE SODIUM; ALCOHOL; SILICON DIOXIDE; XANTHAN GUM; POLYGLYCERYL-6 STEARATE; BUTYLOCTYL SALICYLATE; ALKYL (C12-15) BENZOATE; DISODIUM STEAROYL GLUTAMATE; DOCOSANOL; CETOSTEARYL ALCOHOL; ETHYLHEXYLGLYCERYL BEHENATE; CETYL ALCOHOL; DIISOSTEAROYL POLYGLYCERYL-3 DIMER DILINOLEATE; ETHYLHEXYLGLYCERIN; HYDROXYACETOPHENONE

Eucerin Oil-Control SPF 50 Face Lotion Sunscreen

Active ingredients

Avobenzone, Homosalate, Octisalate, Octocrylene

Purpose

Sunscreen

Uses

■ helps prevent sunburn

■ if used as directed with other sun protection measures (see Directions), decreases the risk of skin cancer and early skin aging caused by the sun

Warnings

For external use only

Do not useon damaged or broken skin

WHEN USING

When using this productkeep out of eyes. Rinse with water to remove.

Stop use and ask a doctor ifrash occurs

Keep out of reach of children.If product is swallowed, get medical help or contact a Poison Control Center right away.

Directions

■ apply liberally 15 minutes before sun exposure

■ reapply at least every 2 hours

■ use a water resistant sunscreen if swimming or sweating

■ Sun Protection Measures.Spending time in the sun increases your risk of skin cancer and early skin aging. To decrease this risk, regularly use a sunscreen with a Broad Spectrum SPF value of 15 or higher and other sun protection measures including:

■ limit time in the sun, especially from 10 a.m. – 2 p.m.

■ wear long-sleeve shirts, pants, hats, and sunglasses

■ children under 6 months: Ask a doctor

Other information

■ protect this product from excessive heat and direct sun

■ may stain or damage some fabrics or surfaces

■ store this product in upright position

Inactive ingredients

Water, Alcohol Denat., Butyloctyl Salicylate, Silica, C12-15 Alkyl Benzoate, Polyglyceryl-6 Stearate, Sodium Stearoyl Glutamate, Diisostearoyl Polyglyceryl-3 Dimer Dilinoleate, Behenyl Alcohol, Butylene Glycol Dicaprylate/Dicaprate, Cetearyl Alcohol, Copernicia Cerifera (Carnauba) Wax, Dibutyl Adipate, L-Carnitine, Glycyrrhiza Inflata Root Extract, Glycyrrhetinic Acid, Tocopherol, Dimethicone, Silica Dimethyl Silylate, Diethylhexyl Syringylidenemalonate, Ethylcellulose, Glyceryl Behenate, Polyglyceryl-6 Octastearate, Phenoxyethanol, Glycerin, Xanthan Gum, Ethylhexylglycerin, Disodium EDTA, Hydroxyacetophenone, Polyglyceryl-6 Behenate, Cetyl Alcohol, Sodium Ascorbyl Phosphate

Questions?

1-800-227-4703

PACKAGE LABEL

Eucerin®

Oil Control

+Oil Absorbing Minerals

Lightweight Sunscreen Lotion For Fact

50 Broad Spectrum SPF 50

Won't Clog Pores

Hypoallergenic | Fragrance Free

No Oxybenzone & Octinoxate

5 AOX SHIELD

Antioxidant Defense

Developed With Dermatologists

2.5 FL OZ (75 mL)